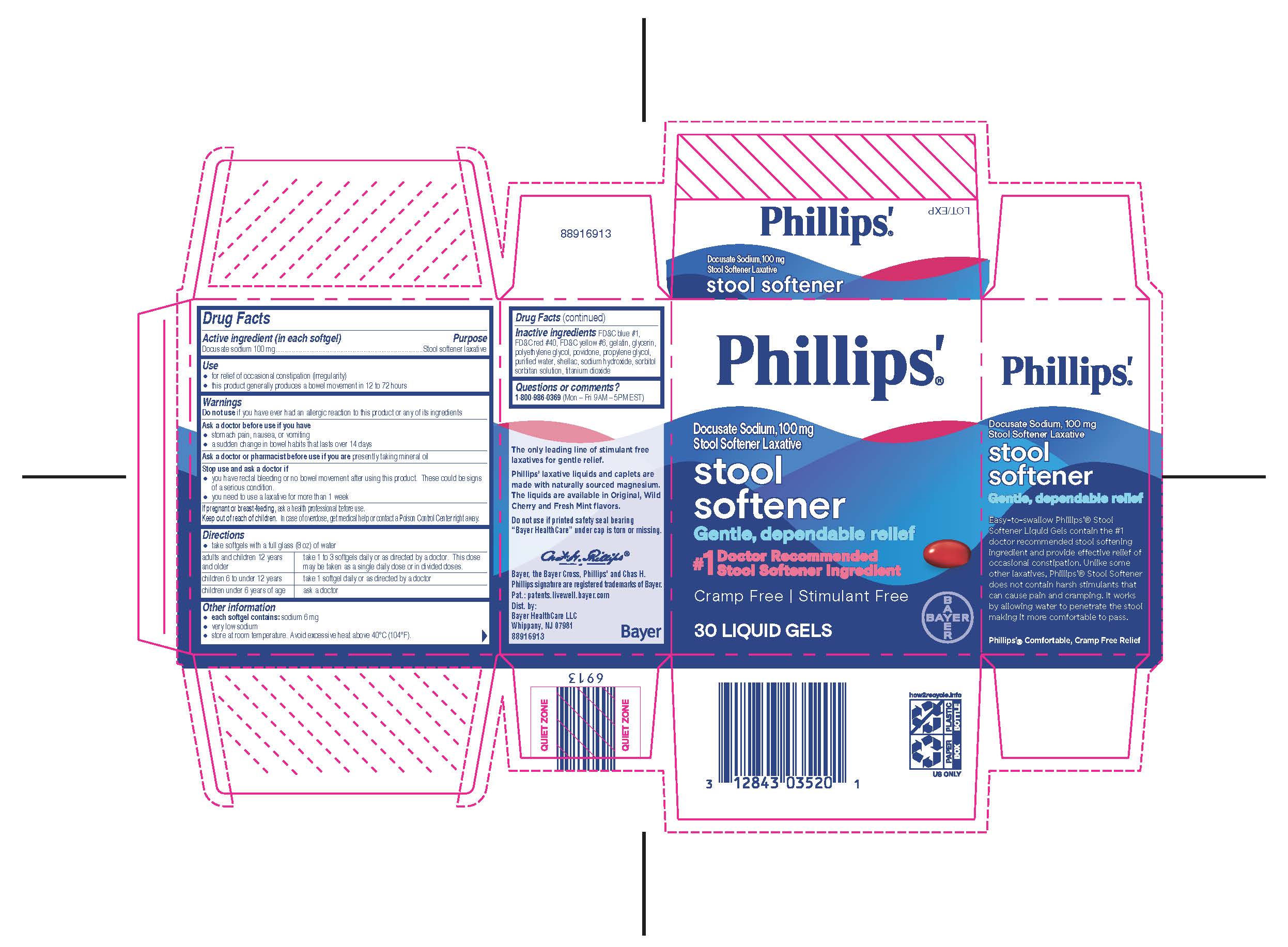 DRUG LABEL: Phillips Stool Softener
NDC: 0280-1012 | Form: CAPSULE, LIQUID FILLED
Manufacturer: Bayer HealthCare LLC.
Category: otc | Type: HUMAN OTC DRUG LABEL
Date: 20251204

ACTIVE INGREDIENTS: DOCUSATE SODIUM 100 mg/1 1
INACTIVE INGREDIENTS: PROPYLENE GLYCOL; WATER; SHELLAC; SODIUM HYDROXIDE; TITANIUM DIOXIDE; FD&C BLUE NO. 1; FD&C RED NO. 40; FD&C YELLOW NO. 6; GELATIN; GLYCERIN; POLYETHYLENE GLYCOL, UNSPECIFIED; POVIDONE; SORBITOL; SORBITAN

Phillips®' Stool Softener Liquid Gels

Drug Facts

Active ingredient (in each softgel)

Docusate sodium 100 mg

Purpose

Stool softener laxative

Use

- for relief of occasional constipation (irregularity)
- this product generally produces a bowel movement in 12 to 72 hours

Warnings

Do not use if you have ever had an allergic reaction to this product or any of its ingredients.

Ask a doctor before use if you have

- stomach pain, nausea, or vomiting
- a sudden change in bowel habits that lasts over 14 days

Ask a doctor or pharmacist before use if you are presently taking mineral oil

Stop use and ask a doctor if

- you have rectal bleeding or no bowel movement after using this product. These could be signs of a serious condition.
- you need to use a laxative for more than 1 week

PREGNANCY OR BREAST FEEDING

If pregnant or breast-feeding, ask a health professional before use.

Keep out of reach of children. In case of overdose, get medical help or contact a Poison Control Center right away.

Directions

- take softgels with a full glass (8 oz) of water

adults and children 12 years and older | take 1 to 3 softgels daily or as directed by a doctor. This dose may be taken as a single daily dose or in divided doses.
children 6 to under 12 years | take 1 softgel daily or as directed by a doctor
children under 6 years of age | ask a doctor

Other information

- each softgel contains: sodium 6 mg
- very low sodium
- store at room temperature. Avoid excessive heat 40°C (104°F).

Inactive ingredients

FD&C blue #1, FD&C red #40, FD&C yellow #6, gelatin, glycerin, polyethylene glycol, povidone, propylene glycol, purified water, shellac, sodium hydroxide, sorbitol sorbitan solution, titanium dioxide

Questions or comments?

1-800-986-0369 (Mon – Fri 9AM – 5PM EST) or www.bayercare.com